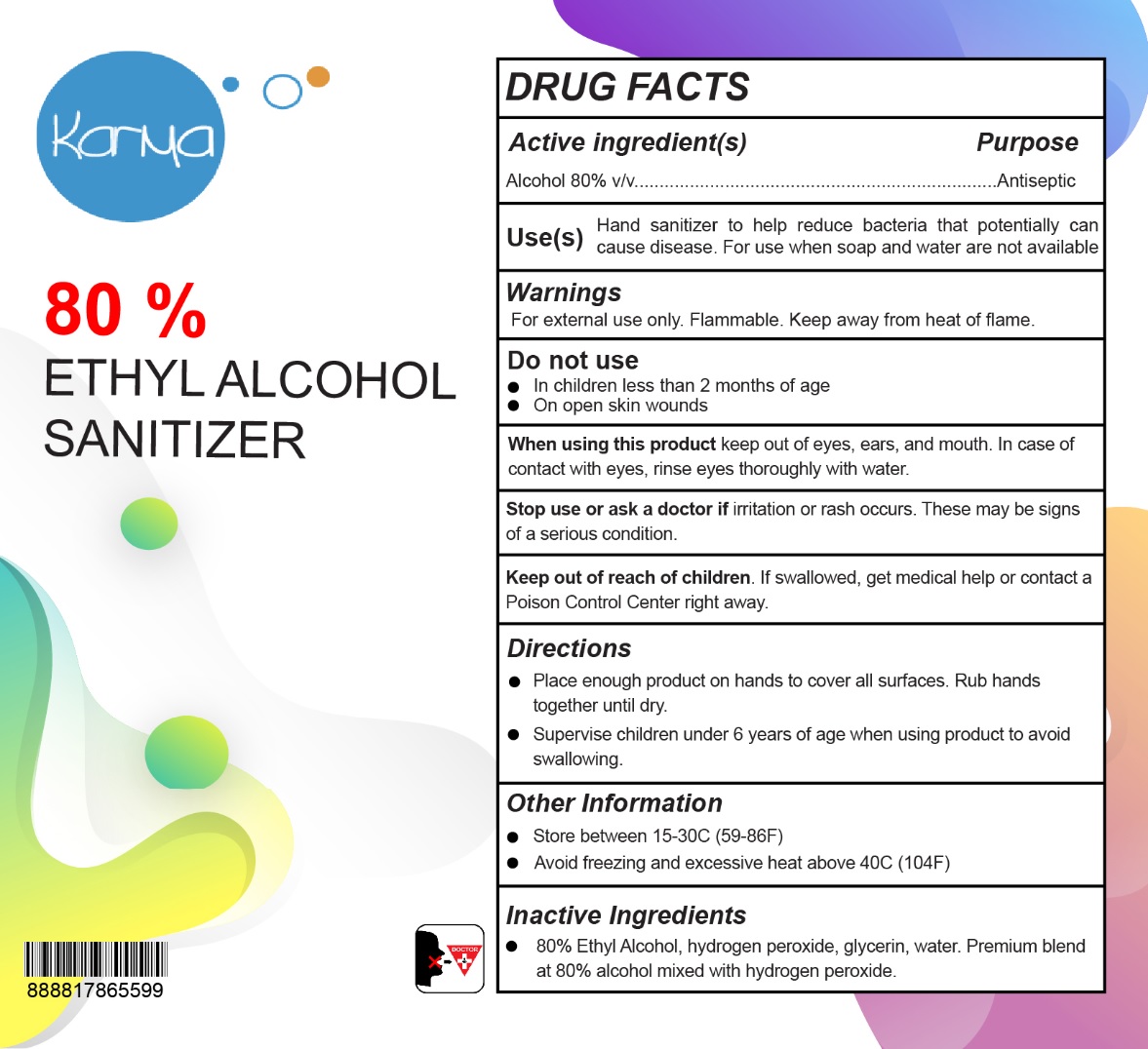 DRUG LABEL: Karma 80 % ETHYL ALCOHOL SANITIZER
NDC: 78608-808 | Form: LIQUID
Manufacturer: STAR VALLEY RESEARCH, LLC DBA United Sanitizer
Category: otc | Type: HUMAN OTC DRUG LABEL
Date: 20200603

ACTIVE INGREDIENTS: ALCOHOL 80 L/100 L
INACTIVE INGREDIENTS: HYDROGEN PEROXIDE; GLYCERIN; WATER

Karma 80 % ETHYL ALCOHOL SANITIZER

Active ingredient(s)

Alcohol 80% v/v

Purpose

Antiseptic

INDICATIONS AND USAGE

Use(s) Hand sanitizer to help reduce bacteria that potentially can cause disease. For use when soap and water are not available.

Warnings

For external use only. Flammable. Keep away from heat of flame.

Do not use

- In children less than 2 months of age
- On open skin wounds

When using this product keep out of eyes, ears, and mouth. In case of contact with eyes, rinse eyes thoroughly with water.

Stop use and ask a doctor if irritation or rash occurs. These may be signs of a serious condition.

Keep out of reach of children. If swallowed, get medical help or contact a Poison Control Center right away.

Directions

- Place enough product on hands to cover all surfaces. Rub hands together until dry.
- Supervise children under 6 years of age when using product to avoid swallowing.

Other Information

- Store between 15-30C (59-86F)
- Avoid freezing and excessive heat above 40C (104F)

Inactive Ingredients

- 80% Ethyl Alcohol, hydrogen peroxide, glycerin, water. Premium blend at 80% alcohol mixed with hydrogen peroxide.